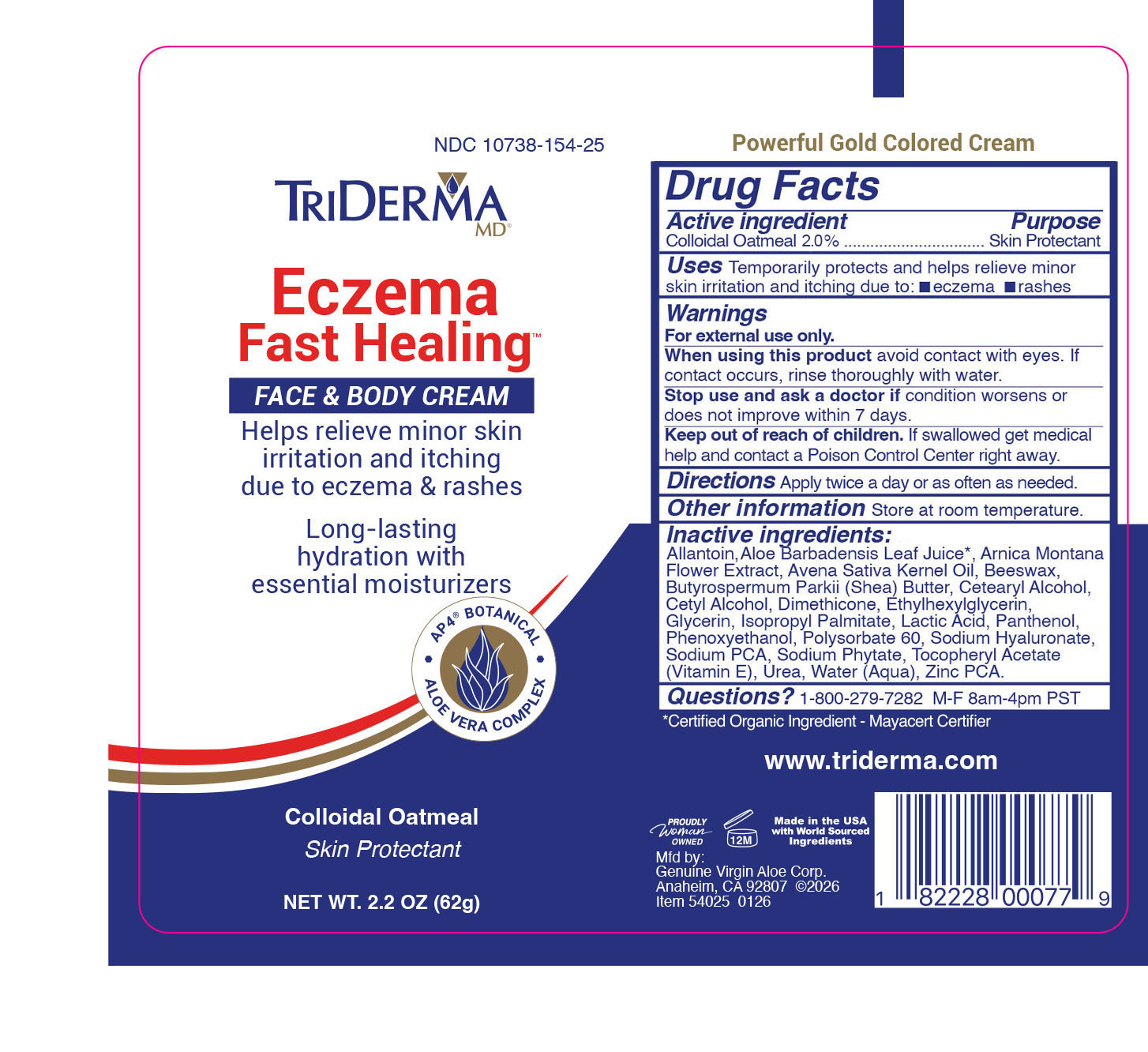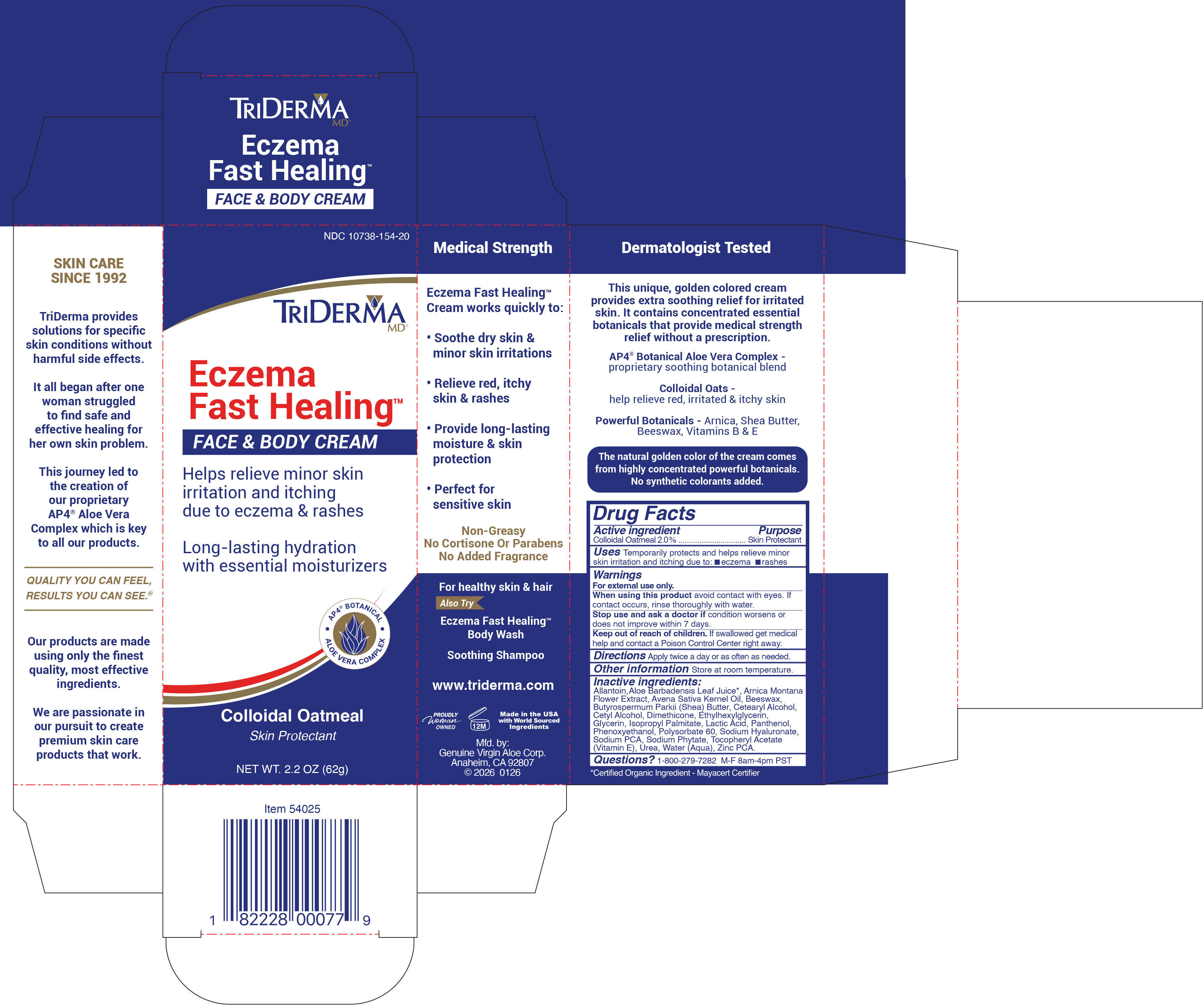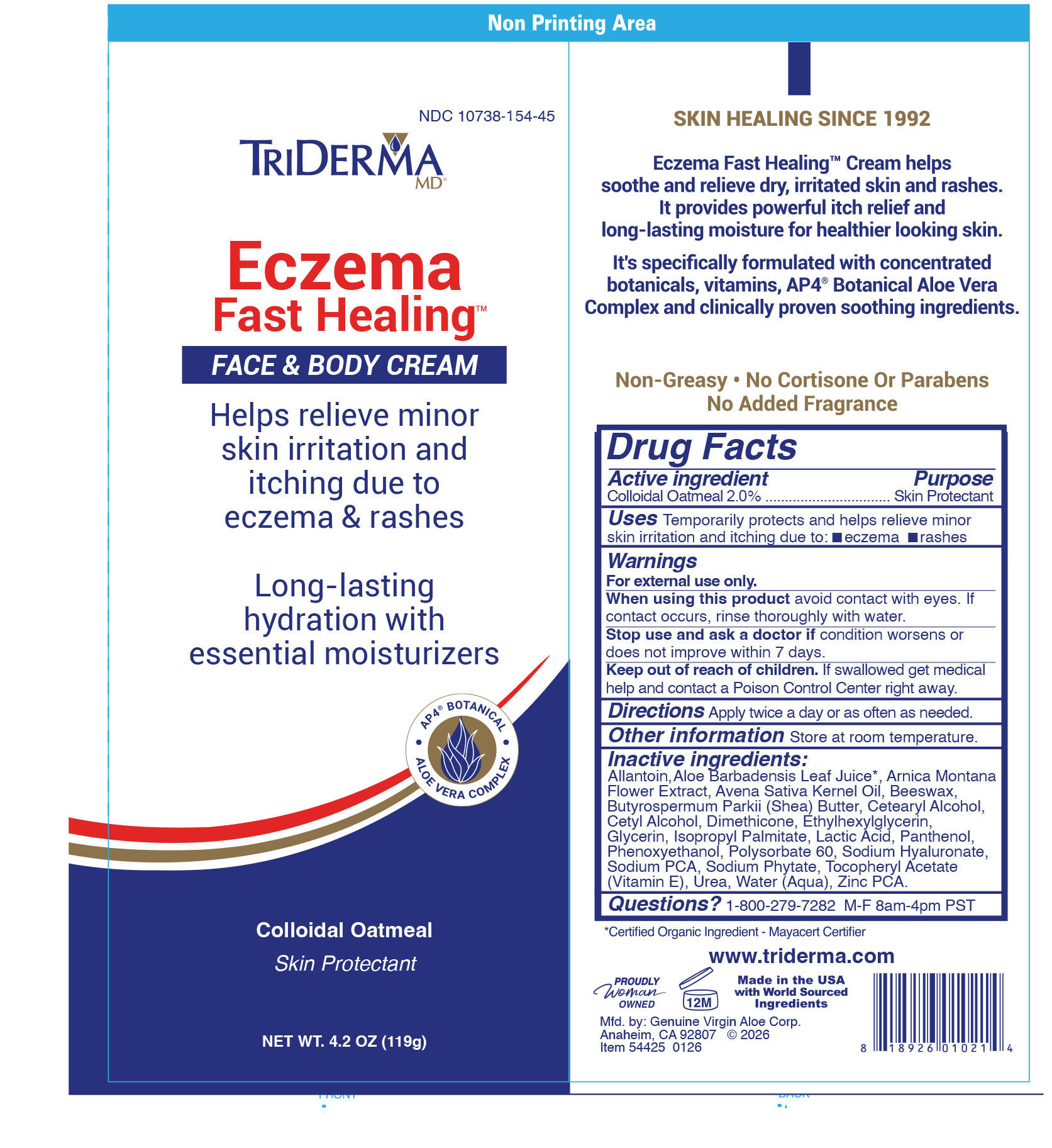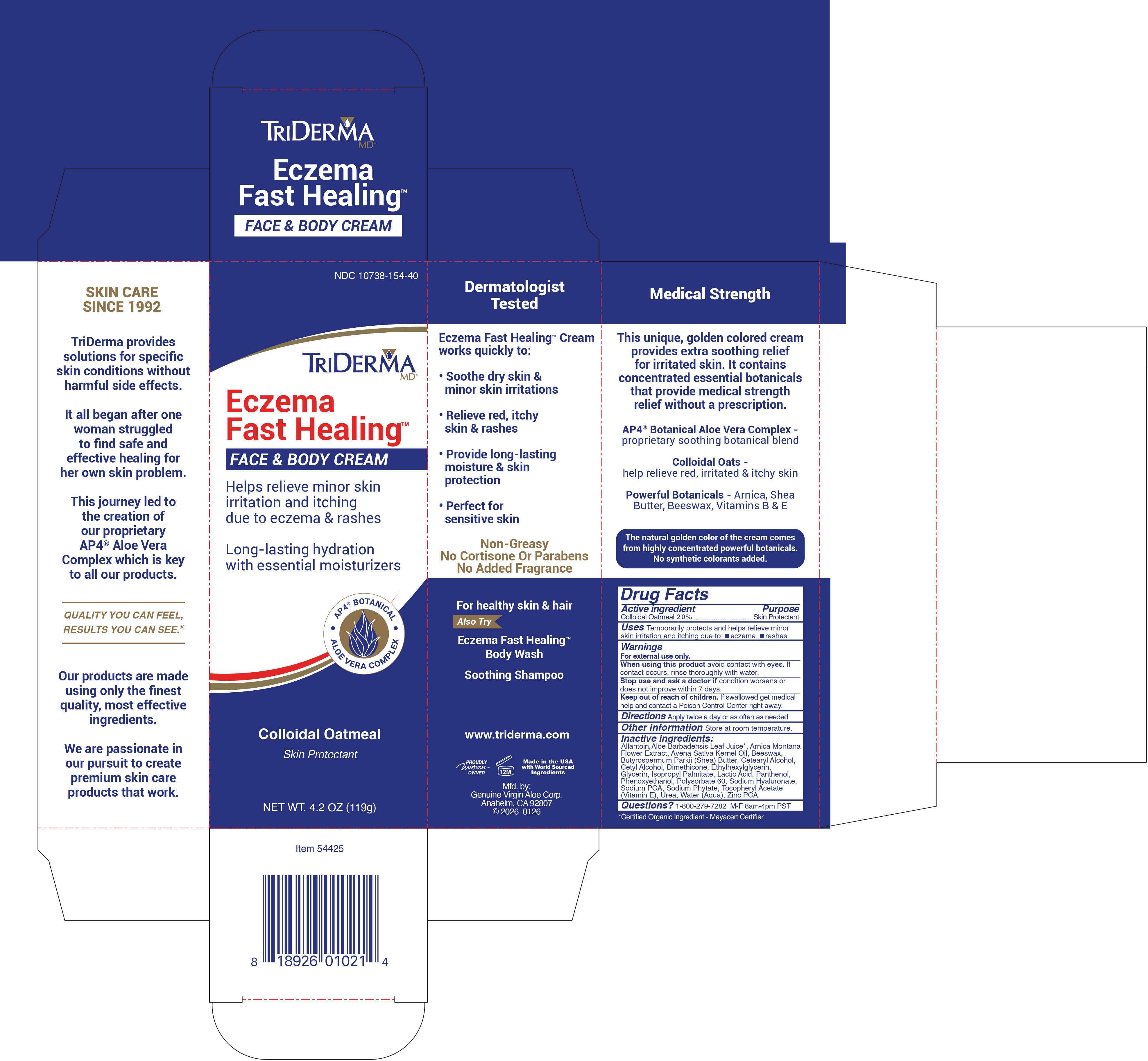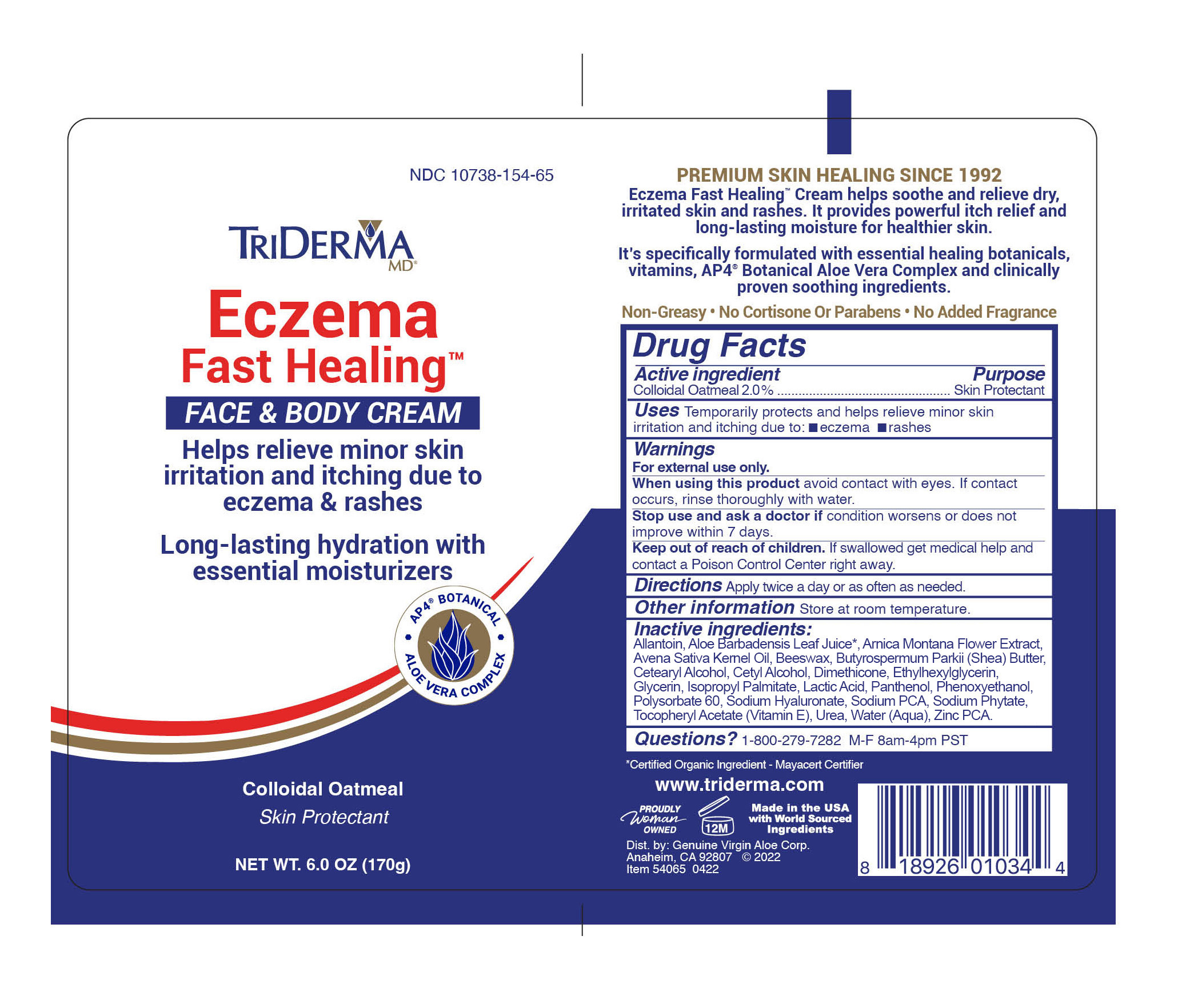 DRUG LABEL: TriDerma Eczema Fast Healing Face Body
NDC: 10738-154 | Form: CREAM
Manufacturer: Genuine Virgin Aloe Corporation
Category: otc | Type: HUMAN OTC DRUG LABEL
Date: 20260130

ACTIVE INGREDIENTS: OATMEAL 2 g/100 g
INACTIVE INGREDIENTS: DIMETHICONE 100; BEESWAX; ALOE VERA LEAF JUICE; SHEA BUTTER; ALLANTOIN; ARNICA MONTANA FLOWER; AVENA SATIVA (OAT) KERNEL OIL; PANTHENOL; CETYL ALCOHOL; SODIUM PCA; ISOPROPYL PALMITATE

TriDerma Eczema Fast Healing Face Body Cream

WARNINGS

For external use only

PURPOSE

Skin Protectant

DIRECTIONS

apply twice a day or as often as needed.

INACTIVE INGREDIENTS

Allantoin, Aloe Barbadensis Leaf Juice*, Arnica Montana Flower Extract, Avena Sativa Kernel Oil, Butyrospermum Parkii (Shea) Butter, Cera Alba (Beeswax), Cetearyl Alcohol, Cetyl Alcohol, Dimethicone, Ethylhexylglycerin, Glycerin, Isopropyl Palmitate, Lactic Acid, Panthenol (Pro-Vitamin B5), Phenoxyethanol, Polysorbate 60, Sodium Hyaluronate, Sodium PCA, Sodium Phytate, Tocopheryl Acetate (Vitamin E), Urea, Water, Zinc PCA

*Certified Organic Ingredient - Mayacert Certifier

ACTIVE INGREDIENT

Colloidal Oatmeal 2%

USES

temporarily protects and helps relieve minor skin irritation and itching due to: •eczema •rashes

DO NOT USE:

on deep puncture wounds, on infections, on lacerations

WHEN USING THIS PRODUCT:

do not get into eyes

KEEP OUT OF REACH OF CHILDREN

if swallowed get medical help and contact a Poison Control Center right away.

STOP USE AND ASK A DOCTOR IF:

condition worsens or does not improve within 7 days.